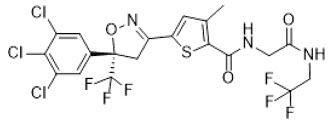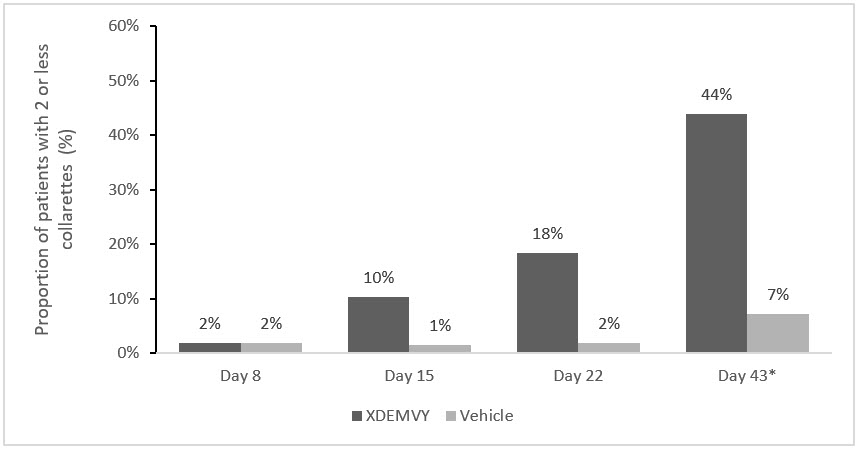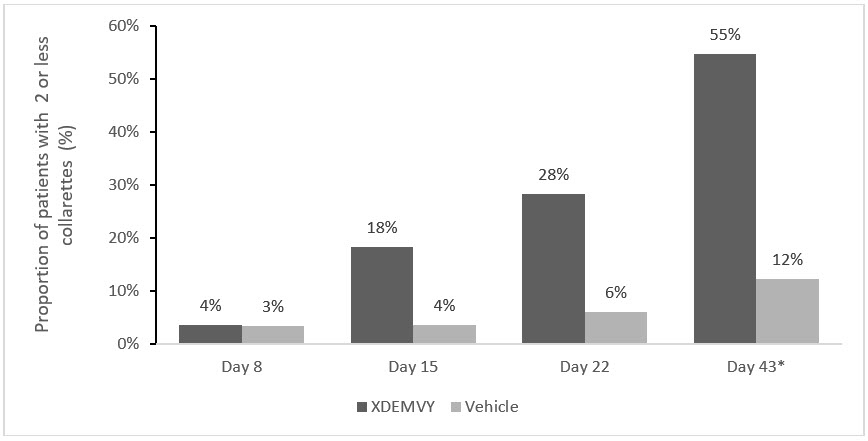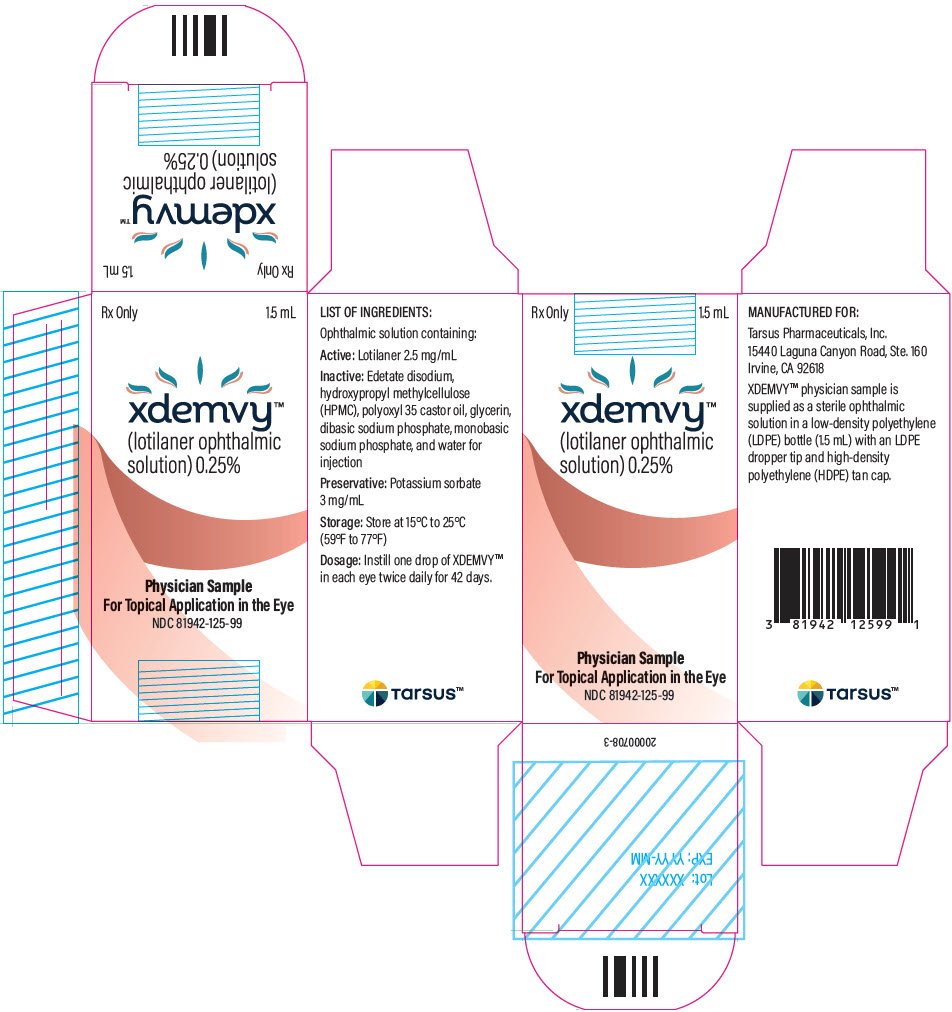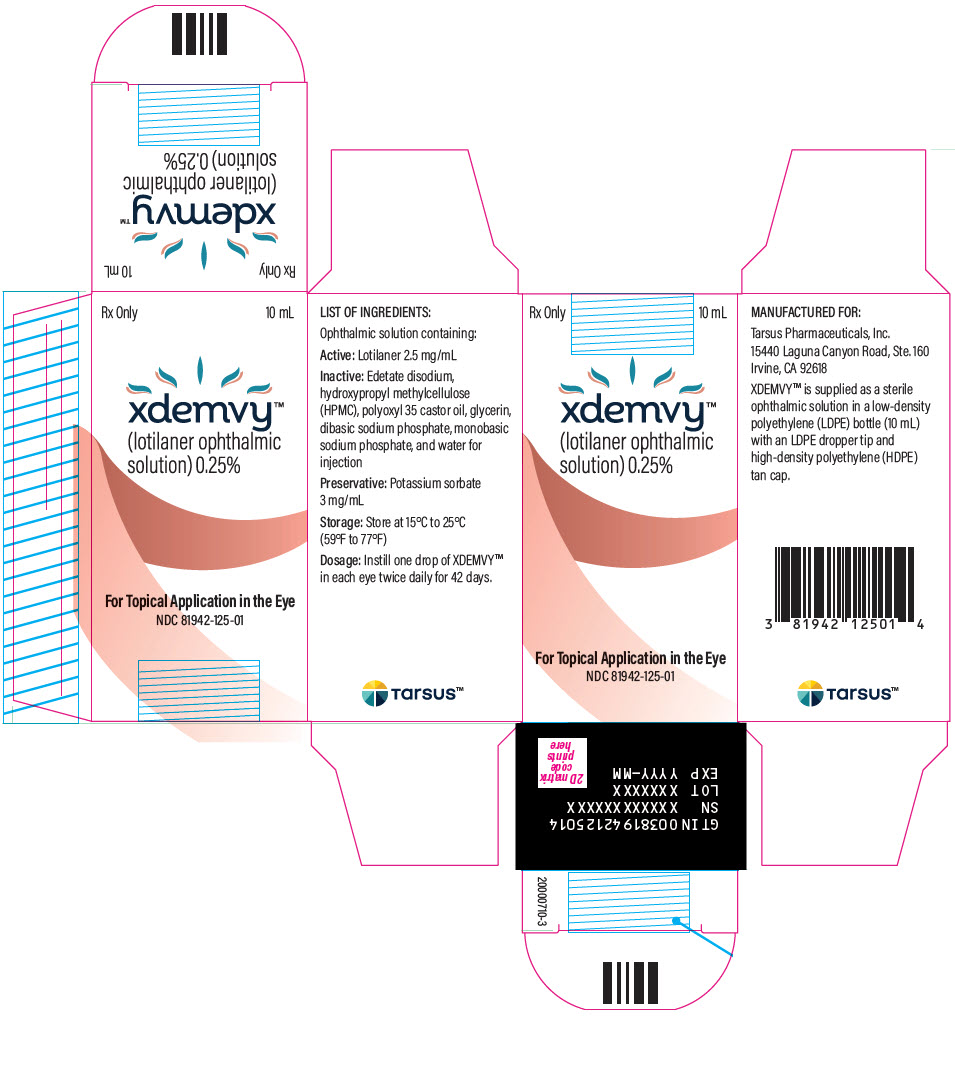 DRUG LABEL: XDEMVY
NDC: 81942-125 | Form: SOLUTION/ DROPS
Manufacturer: Tarsus Pharmaceuticals, Inc.
Category: prescription | Type: HUMAN PRESCRIPTION DRUG LABEL
Date: 20240810

ACTIVE INGREDIENTS: LOTILANER 2.5 mg/1 mL

HIGHLIGHTS OF PRESCRIBING INFORMATION

These highlights do not include all the information needed to use XDEMVY safely and effectively. See full prescribing information for XDEMVY.
XDEMVY™ (lotilaner ophthalmic solution) 0.25%, for topical ophthalmic use
Initial U.S. Approval: 2023

1 INDICATIONS AND USAGE

XDEMVY is an ectoparasiticide (anti-parasitic) indicated for the treatment of Demodex blepharitis. (1)

2 DOSAGE AND ADMINISTRATION

Instill one drop of XDEMVY in each eye twice daily (approximately 12 hours apart) for 6 weeks. (2)

3 DOSAGE FORMS AND STRENGTHS

Ophthalmic solution containing lotilaner 0.25%. (3)

4 CONTRAINDICATIONS

None. (4)

6 ADVERSE REACTIONS

The most common adverse reaction was instillation site stinging and burning (10%). (6.1)

To report SUSPECTED ADVERSE REACTIONS, contact Tarsus Pharmaceuticals at 1-888-421-4002 or FDA at 1-800-FDA-1088 or www.fda.gov/medwatch.

FULL PRESCRIBING INFORMATION

1 INDICATIONS AND USAGE

XDEMVY is indicated for the treatment of Demodex blepharitis.

2 DOSAGE AND ADMINISTRATION

Instill one drop of XDEMVY in each eye twice daily (approximately 12 hours apart) for 6 weeks. If more than one topical ophthalmic drug is being used, the drugs should be administered at least five (5) minutes apart. If one dose is missed, treatment should continue with the next scheduled dose.

3 DOSAGE FORMS AND STRENGTHS

XDEMVY (lotilaner ophthalmic solution) is provided as an ophthalmic solution containing lotilaner 0.25% (2.5 mg/mL).

4 CONTRAINDICATIONS

None.

5 WARNINGS AND PRECAUTIONS

5.1 Risk of Contamination

Do not allow the tip of the dispensing container to contact the eye, surrounding structures, fingers, or any other surface in order to minimize contamination of the solution. Serious damage to the eye and subsequent loss of vision may result from using contaminated solutions .

5.2 Use with Contact Lenses

Contact lenses should be removed prior to instillation of XDEMVY and may be reinserted 15 minutes following its administration.

6 ADVERSE REACTIONS

6.1 Clinical Trials Experience

Because clinical studies are conducted under widely varying conditions, adverse reaction rates observed in the clinical trials of a drug cannot be directly compared to rates in the clinical trials of another drug and may not reflect the rates observed in practice.

XDEMVY was evaluated in 833 patients with Demodex blepharitis in two randomized, double-masked, vehicle-controlled studies (Saturn-1 and Saturn-2) with 42 days of treatment. The most common ocular adverse reaction observed in controlled clinical studies with XDEMVY was instillation site stinging and burning which was reported in 10% of patients. Other ocular adverse reactions reported in less than 2% of patients were chalazion/hordeolum and punctate keratitis.

8 USE IN SPECIFIC POPULATIONS

8.1 Pregnancy

Risk Summary

There are no available data on XDEMVY use in pregnant women to inform any drug associated risk; however, systemic exposure to lotilaner from ocular administration is low [see Clinical Pharmacology (12.3)] . In animal reproduction studies, lotilaner did not produce malformations at clinically relevant doses.

Data

Animal Data

In an oral embryofetal developmental study in pregnant rats dosed during organogenesis from gestation days 6-19, increased post-implantation loss, reduced fetal pup weight, and incomplete skeletal ossification were observed at 50 mg/kg/day (approximately 1390 times the recommended human ophthalmic dose (RHOD) on a body surface area basis) in the presence of maternal toxicity (i.e., decreased body weight and food consumption). A rare malformation of situs inversus of the thoracic and abdominal viscera occurred in 1 fetus from a pregnant rat receiving 50 mg/kg/day; whether this finding was treatment-related could not be excluded. No maternal or embryofetal toxicity was observed at 18 mg/kg/day (approximately 501 times the RHOD on a body surface area basis). In an oral embryofetal development study in pregnant rabbits dosed during organogenesis from gestation days 7-19, no embryofetal toxicity or teratogenic findings were observed at 20 mg/kg/day (approximately 580-times the RHOD on an AUC basis), even in the presence of maternal toxicity (i.e., decreased food consumption and body weight).

In an oral two-generation reproductive toxicity study, F0 male and female rats were administered lotilaner at doses up to 40 mg/kg/day for 10 weeks before pairing and during the 2-week pairing period (3 weeks for males). Dosing for F0 females continued through lactation day 22. F1 male and female rats were administered lotilaner at 1 and 5 mg/kg/day post-weaning from day 23 for 10 weeks before pairing and during the 2-week pairing period (3 weeks for males). Dosing for F1 parenteral females continued through lactation day 22. There were no clear adverse effects on the F1 generation, and a slightly lower mean body weight during lactation was noted for F2 pups at 5 mg/kg/day. The no observed adverse effect level (NOAEL) was determined to be 5 mg/kg/day (approximately 139 times the RHOD on a body surface area basis).

8.2 Lactation

Risk Summary

There are no data on the presence of XDEMVY in human milk, the effects on the breastfed infant, or the effects on milk production. However, systemic exposure to lotilaner following 6 weeks of topical ocular administration is low and is >99% plasma protein bound [see Clinical Pharmacology (12.3)] , thus it is not known whether measurable levels of lotilaner would be present in maternal milk following topical ocular administration. The developmental and health benefits of breastfeeding should be considered along with the mother's clinical need for XDEMVY and any potential adverse effects on the breast-fed child from XDEMVY.

8.4 Pediatric Use

Safety and effectiveness in pediatric patients below the age of 18 years have not been established.

8.5 Geriatric Use

No overall differences in safety or effectiveness have been observed between elderly and other adult patients.

11 DESCRIPTION

Lotilaner is a member of the isoxazoline family of compounds. Its chemical name is 2-Thiophenecarboxamide, 5-[(5S)-4,5-dihydro-5-(3,4,5-trichlorophenyl)-5-(trifluoromethyl)-3-isoxazolyl]-3-methyl-N-[2-oxo-2-[(2,2,2-trifluoroethyl)amino]ethyl]-2-thiophenecarboxamide. The molecular formula is C20H14Cl3F6N3O3S. The molecular weight is 596.76 g/mol. The chemical structure is:

XDEMVY is a sterile, preserved, multi-dose, slightly yellowish, slightly opalescent, topical ophthalmic solution containing lotilaner, 0.25% as the active ingredient. It is preserved with potassium sorbate and contains the following additional inactive ingredients: edetate disodium, hydroxypropyl methylcellulose (HPMC), polyoxyl 35 castor oil, glycerin, dibasic sodium phosphate, monobasic sodium phosphate, and water for injection.

12 CLINICAL PHARMACOLOGY

12.1 Mechanism of Action

Lotilaner is a gamma-aminobutyric acid (GABA)-gated chloride channel inhibitor selective for mites. Inhibition of these GABA chloride channels causes a paralytic action in the target organism leading to its death. Lotilaner is not an inhibitor of mammalian GABA mediated chloride channels when tested at up to 30 µM (18 µg/mL) in vitro(approximately 1100 times the RHOD).

12.3 Pharmacokinetics

The systemic pharmacokinetic profile after topical ocular administration was evaluated in healthy volunteers after single and repeat dose administration. The systemic exposure was evaluated in patients at the end of 6 weeks of treatment.

Absorption

Maximum lotilaner concentration was observed 2 hours after a single ocular administration on Day 1 and 1 hour after the last drug administration on Day 42. In healthy subjects, the peak concentration (Cmax) and total exposure (AUC0-12) of lotilaner in whole blood increased after 42 days of repeated ocular administration from 0.596 to 17.8 ng/mL and from 5.75 to 149 hr•ng/mL for Cmaxand AUC0-12respectively. The effective half-life of lotilaner, which is based on the accumulation ratio over the dosing interval of 12 hours, was 264 hours (11 days). In patients with Demodex blepharitis (n=138) who received XDEMVY twice daily for 42 days, the mean (range) systemic exposure at the end of treatment was 12.0 ng/mL (0.4-46.1 ng/mL).

Distribution

Lotilaner plasma protein binding is high (> 99.9%) in human plasma. The partitioning of lotilaner to human blood cells is approximately 10% (range 0-20%).

Elimination

The effective half-life in healthy subjects, which is based on the accumulation ratio over the dosing interval of 12 hours, is 264 hours (11 days).

Metabolism

Lotilaner is not metabolized by CYP enzymes.

13 NONCLINICAL TOXICOLOGY

13.1 Carcinogenesis, Mutagenesis, Impairment of Fertility

Carcinogenesis

Long-term studies in animals have not been performed to evaluate the carcinogenic potential of lotilaner.

Mutagenesis

Lotilaner was not genotoxic in the following assays: Ames assay for bacterial gene mutation, in vitrochromosomal aberration assay in cultured human peripheral blood lymphocytes, and in vivorat micronucleus test.

Impairment of fertility

In a two-generation study of reproductive performance in rats, F0 male and female rats were administered lotilaner at oral doses of 40 mg/kg/day for 80 days reduced to 20 mg/kg/day for 47-50 supplementary days. Reduced pregnancy rates and decreased implantation rates were observed in F0 females at doses 20 mg/kg/day) (approximately 556 times the RHOD on a body surface area basis), which were also associated with maternal toxicity (i.e., decreased body weight and food consumption). No effects on fertility were observed in F0 females at the dose of 5 mg/kg/day (approximately 139 times the MRHOD on a body surface area basis) .No effects on fertility were observed in F0 males at the oral dose of 20 mg/kg/day (approximately 556 times the RHOD on a body surface area basis), and no effects on fertility were observed in F1 males and females at the oral dose of 5 mg/kg/day (approximately 139 times the RHOD on a body surface area basis).

14 CLINICAL STUDIES

The safety and efficacy of XDEMVY for the treatment of Demodex blepharitis was evaluated in a total of 833 patients (415 of which received XDEMVY) in two 6-week, randomized, multicenter, double-masked, vehicle-controlled studies (Saturn-1 and Saturn-2). Patients with Demodex blepharitis were randomized to either XDEMVY or Vehicle at a 1:1 ratio dosed twice daily in each eye.

Efficacy was demonstrated by improvement in lids (reduction of collarettes to no more than 2 collarettes per upper lid) in each study (Saturn-1 and Saturn-2) (see Figure 1and Figure 2) by Day 43.

Figure 1. Saturn-1: Proportion of patients with 2 or less collarettes for the upper eyelid

*Day 43 Primary Endpoint; XDEMVY N=209, Vehicle N=204, p-value <0.01

Figure 2. Saturn-2: Proportion of patients with 2 or less collarettes for the upper eyelid

*Day 43 Primary Endpoint; XDEMVY N=193, Vehicle N=200, p-value <0.01

The endpoints of mite eradication (mite density of 0 mites/lash) and erythema cure (Grade 0) of XDEMVY vs. Vehicle demonstrated statistically significant improvement at Day 43 across both Saturn-1 (Table 1) and Saturn-2 (Table 2) studies.

Table 1: Proportion of patients with eradication of Demodex mites and erythema cure in the analysis eye at Day 43 in Saturn-1
 | XDEMVY (N=212) | Vehicle (N=209) | p-value
Mite Eradication | 68% | 17% | < 0.01
Erythema Cure | 19% | 7% | < 0.01

Table 2: Proportion of patients with eradication of Demodex mites and erythema cure in the analysis eye at Day 43 in Saturn-2
 | XDEMVY (N=203) | Vehicle (N=209) | p-value
Mite Eradication | 50% | 14% | < 0.01
Erythema Cure | 30% | 9% | < 0.01

16 HOW SUPPLIED/STORAGE AND HANDLING

XDEMVY is supplied as a sterile ophthalmic solution in a white, opaque, low-density polyethylene (LDPE) multiple-dose bottle with a LDPE dropper tip and tan high-density polyethylene (HDPE) cap.

10 mL fill in a 11 mL container | NDC # 81942-125-01

Storage

Store at 15°C to 25°C (59°F to 77°F). After opening the XDEMVY bottle, it can be used until the expiration date on the bottle.

17 PATIENT COUNSELING INFORMATION

Handling the Container

Instruct patients to avoid allowing the tip of the dispensing container to contact the eye, surrounding structures, fingers, or any other surface in order to minimize contamination of the solution. Serious damage to the eye and subsequent loss of vision may result from using contaminated solutions .

When to Seek Physician Advice

Advise patients that if they develop an intercurrent ocular condition (e.g., trauma or infection), have ocular surgery, or develop any ocular reactions, particularly conjunctivitis and eyelid reactions, they should immediately seek their physician's advice concerning the continued use of XDEMVY.

Use with Contact Lenses

Advise patients that XDEMVY contains potassium sorbate, which may discolor soft contact lenses. Contact lenses should be removed prior to instillation of XDEMVY and may be reinserted 15 minutes following its administration.

Use with Other Ophthalmic Drugs

Advise patients that if more than one topical ophthalmic drug is being used, the drugs should be administered at least 5 minutes between applications.

Missed Dose

Advise patients that if one dose is missed, treatment should continue with the next dose.

XDEMVY and/or methods of use thereof may be covered by one or more of the patents listed at www.tarsusrx.com/patents

XDEMVY is a trademark of Tarsus Pharmaceuticals, Inc.

Manufactured for: Tarsus Pharmaceuticals, Inc., Irvine, CA 92618

PRINCIPAL DISPLAY PANEL - 1.5 mL Bottle Carton

Rx Only
1.5 mL

xdemvy™
(lotilaner ophthalmic
solution) 0.25%

Physician Sample

For Topical Application in the Eye

NDC 81942-125-99

PRINCIPAL DISPLAY PANEL - 10 mL Bottle Carton

Rx Only
10 mL

xdemvy™
(lotilaner ophthalmic
solution) 0.25%

For Topical Application in the Eye

NDC 81942-125-01